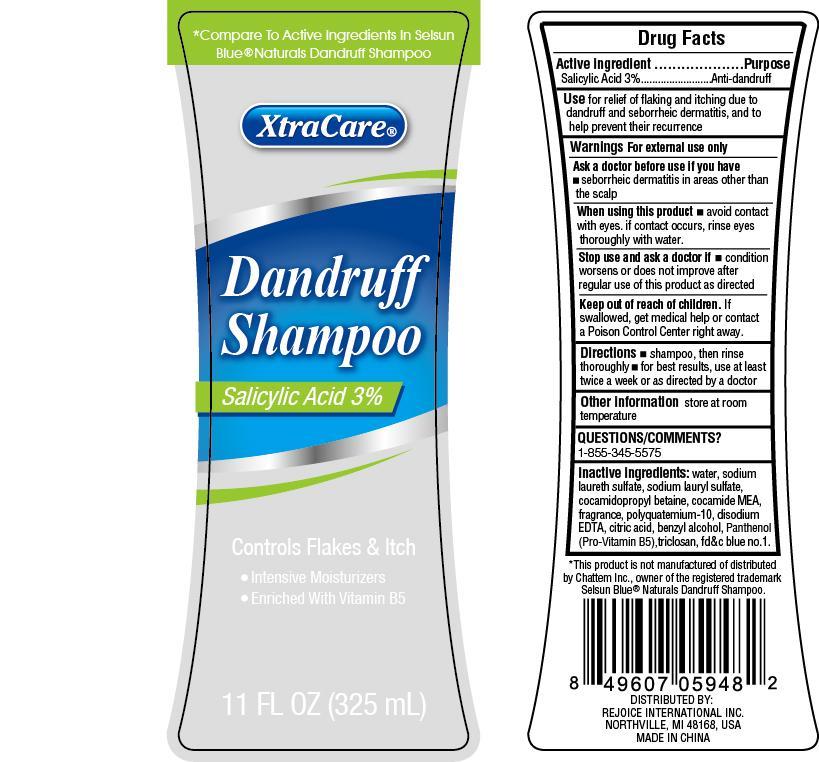 DRUG LABEL: XtraCare Dandruff Hair Wash
NDC: 57337-053 | Form: SHAMPOO
Manufacturer: Rejoice International
Category: otc | Type: HUMAN OTC DRUG LABEL
Date: 20240228

ACTIVE INGREDIENTS: SALICYLIC ACID 10 g/325 g
INACTIVE INGREDIENTS: WATER; SODIUM LAURETH SULFATE; SODIUM LAURYL SULFATE; COCAMIDOPROPYL BETAINE; COCO MONOETHANOLAMIDE; POLYQUATERNIUM-10 (1000 MPA.S AT 2%); EDETATE DISODIUM; CITRIC ACID MONOHYDRATE; BENZYL ALCOHOL; PANTHENOL; TRICLOSAN; FD&C BLUE NO. 1

XtraCare Dandruff Hair Wash

Active Ingredient Purpose

Salicylic Acid 3% ........................... Anti-dandruff

Uses

for relief of flaking and itching due to dandruff and sebhorreic dermatitis, and to help prevent their recurrence

Keep out of reach of children. If swallowed, get medical help or contact a Poison Control Center right away.

INDICATIONS AND USAGE

*compare to active ingredients in Selsun Blue® naturals dandruff shampoo

XtraCare® Dandruff Shampoo Salicylic Acid 3%

Controls Flakes & Itch

- Intensive Moisturizers
- Enriched with Vitamin B5

11 Fl Oz (325 mL)

Warnings

For external use only

Ask a doctor before use if you have

- sebhorreic dermatitis in areas other than the scalp

When using this product

- avoid contact with eyes. If contact occurs, rinse eyes thoroughly with water.

Stop use and ask a doctor if

- condition worsens or does not improve after regular use of this product as directed.

Directions

- shampoo, then rinse thoroughly
- for best results, use at least twice a week or as directed by a doctor

INACTIVE INGREDIENT

Inactive Ingredients: water, sodium laureth sulfate, sodium lauryl sulfate, cocamidopropyl betaine, cocamide MEA, fragrance, polyquaternium-10, disodium EDTA, citric acid, benzyl alcohol, panthenol (pro-vitamin B5), triclosan, fd&c blue no.1

Other Information store at room temperature

Questions/Comments? 1-855-345-5575

*This product is not manufactured or distributed by Chattem, Inc., owner of the registered trademark Selsun Blue® Naturals Dandruff Shampoo.

DISTRIBUTED BY:

REJOICE INTERNATIONAL INC

NORTHVILLE, MI 48168, USA

MADE IN CHINA